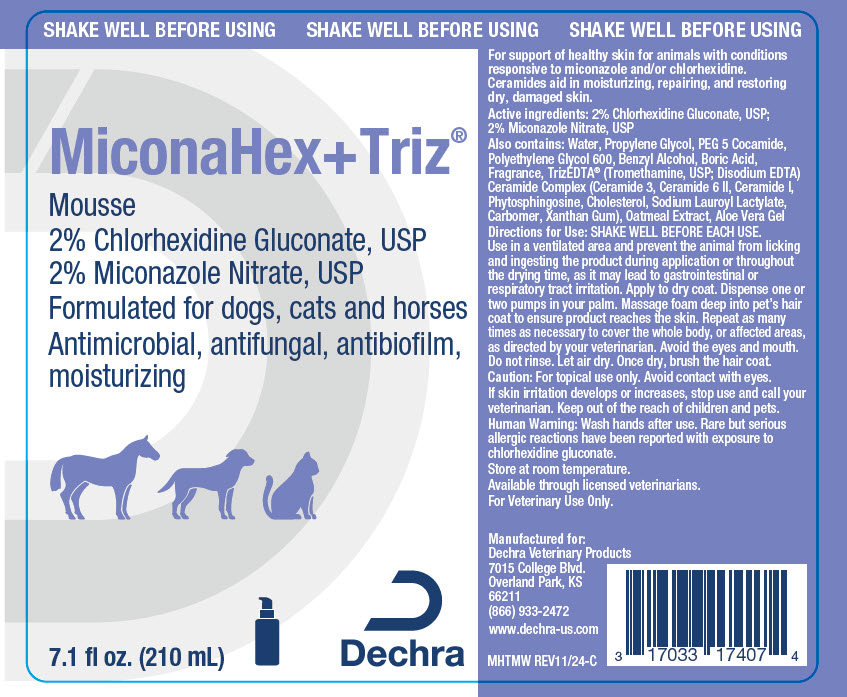 DRUG LABEL: MiconaHex Plus Triz Mousse
NDC: 17033-174 | Form: SPRAY, SUSPENSION
Manufacturer: Dechra Veterinary Products
Category: animal | Type: OTC ANIMAL DRUG LABEL
Date: 20250604

ACTIVE INGREDIENTS: Chlorhexidine Gluconate 20 mg/1 mL; MICONAZOLE NITRATE 20 mg/1 mL

MiconaHex+Triz® Mousse

VETERINARY INDICATIONS

For support of healthy skin for animals with conditions responsive to miconazole and/or chlorhexidine. Ceramides aid in moisturizing, repairing, and restoring dry, damaged skin.

DESCRIPTION

Active ingredients: 2% Chlorhexidine Gluconate, USP; 2% Miconazole Nitrate, USP

Also contains: Water, Propylene Glycol, PEG 5 Cocamide, Polyethylene Glycol 600, Benzyl Alcohol, Boric Acid, Fragrance, TrizEDTA® (Tromethamine, USP; Disodium EDTA) Ceramide Complex (Ceramide 3, Ceramide 6 II, Ceramide I, Phytosphingosine, Cholesterol, Sodium Lauroyl Lactylate, Carbomer, Xanthan Gum), Oatmeal Extract, Aloe Vera Gel

DOSAGE AND ADMINISTRATION

Directions for Use: SHAKE WELL BEFORE EACH USE.

Use in a ventilated area and prevent the animal from licking and ingesting the product during application or throughout the drying time, as it may lead to gastrointestinal or respiratory tract irritation. Apply to dry coat. Dispense one or two pumps in your palm. Massage foam deep into pet's hair coat to ensure product reaches the skin. Repeat as many times as necessary to cover the whole body, or affected areas, as directed by your veterinarian. Avoid the eyes and mouth. Do not rinse. Let air dry. Once dry, brush the hair coat.

WARNINGS

Caution: For topical use only. Avoid contact with eyes.

If skin irritation develops or increases, stop use and call your veterinarian. Keep out of the reach of children and pets.

SAFE HANDLING WARNING

Human Warning: Wash hands after use. Rare but serious allergic reactions have been reported with exposure to chlorhexidine gluconate.

STORAGE AND HANDLING

Store at room temperature.

Available through licensed veterinarians.

For Veterinary Use Only.

Manufactured for:
Dechra Veterinary Products
7015 College Blvd.
Overland Park, KS 66211
(866) 933-2472

www.dechra-us.com

MHTMW REV11/24-C

PRINCIPAL DISPLAY PANEL - 210 mL Bottle Label

SHAKE WELL BEFORE USING

MiconaHex+Triz®
Mousse

2% Chlorhexidine Gluconate, USP
2% Miconazole Nitrate, USP

Formulated for dogs, cats and horses
Antimicrobial, antifungal, antibiofilm,
moisturizing

7.1 fl oz. (210 mL)

Dechra